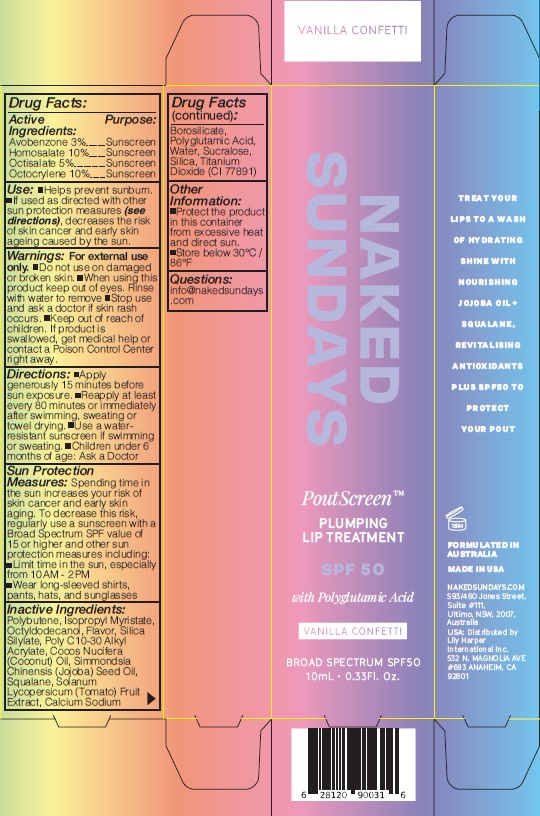 DRUG LABEL: Naked Sundays PoutScreen Plumping Lip Treatment VANILLA CONFETTI 10mL
NDC: 81104-250 | Form: LIQUID
Manufacturer: NAKED SUNDAYS PTY LTD
Category: otc | Type: HUMAN OTC DRUG LABEL
Date: 20250322

ACTIVE INGREDIENTS: HOMOSALATE 10 g/100 mL; OCTOCRYLENE 10 g/100 mL; AVOBENZONE 3 g/100 mL; OCTISALATE 5 g/100 mL
INACTIVE INGREDIENTS: ACRYLATES/C10-30 ALKYL ACRYLATE CROSSPOLYMER (60000 MPA.S); SUCRALOSE; POLYBUTENE (1400 MW); SILICA DIMETHYL SILYLATE; OCTYLDODECANOL; WATER; COCONUT OIL; POLYGLUTAMIC ACID (1200 MW); SQUALANE; JOJOBA OIL; TITANIUM DIOXIDE; ISOPROPYL MYRISTATE; SOLANUM LYCOPERSICUM; CALCIUM SODIUM BOROSILICATE; SILICON DIOXIDE

Naked Sundays PoutScreen Plumping Lip Treatment VANILLA CONFETTI 10mL

ACTIVE INGREDIENTS

AVOBENZONE 3%

HOMOSALATE 10%

OCTISALATE 5%

OCTOCRYLENE 10%

Purpose

Sunscreen

USES

Uses: Helps prevent sunburn. If used as
directed with other sun protection measures
(see directions), decreases the risk of skin
cancer and early skin ageing caused by the sun.

WARNINGS

Warnings: For external use only. Do not use
on damaged or broken skin Avoid prolonged
sun exposure. If it gets in your eyes, wash well
with water. Keep out of reach of children.
Stop use and ask a doctor if rashes occur.
If product is swallowed, get medical help or
contact a Poison Control Center right away.

Keep out of reach of children. If product is swallowed, get medical help or contact a Poison Control Center right away.

DIRECTIONS

- SPRAY 7 TIMES WITH MOUTH AND LIPS CLOSED 8-10" AWAY FROM FACE 15 MINUTES BEFORE SUN EXPOSURE.
- Reapply after 80 minutes of swimming or sweating.
- Reapply immediately after towel drying.
- Reapply at least every 2 hours.
- Children under 3 years of age: Ask a doctor.

SUN PROTECTION MEASURES:

Spending time in the sun increases your risk of skin cancer and early skin aging. To decrease this risk, regularly use a sunscreen with a Broad Spectrum SPF value of 15 or higher and other sun protection measures including:

- Limit time in the sun, especially from 10.00AM - 2.00PM
- Wear long-sleeved shirts, pants, hats, and sunglasses

INACTIVE INGREDIENTS

Polybutene, Isopropyl Myristate, Octyldodecanol, Poly C10-30
Alkyl Acrylate, Silica Silylate Flavor, Cocos Nucifera
(Coconut) Oil,Silica, , Titanium Dioxide (Cl 77891), Simmondsia Chinensis (Jojoba) Seed Oil, Squalane, Solanum Lycopersicum
(Tomato) Fruit Extract, Calcium Sodium Borosilicate
Polyglutamic Acid Water, Sucralose

OTHER INFORMATION

Other Information: Protect this product
from excess heat and direct sun. Store below
30°C / 86°F.

USER SAFETY WARNINGS

Directions: "Apply generously 15 minutes before sun exposure. Reapply at least every 80 minutes or immediately after swimming, sweating or towel drying. Use a water- resistant sunscreen if swimming
or sweating. "Children under 6' months of age: Ask a Doctor

Sun Protection Measures: Spending time in the sun increases your risk of skin cancer and early skin aging. To decrease this risk, regularly use a sunscreen with a Broad Spectrum SPF value of 15 or higher and other sun protection measures including:
•Limit time in the sun, especially from 10AM - 2PM
•Wear long-sleeved shirts, pants, hats, and sunglasses

PURPOSE

Sunscreen